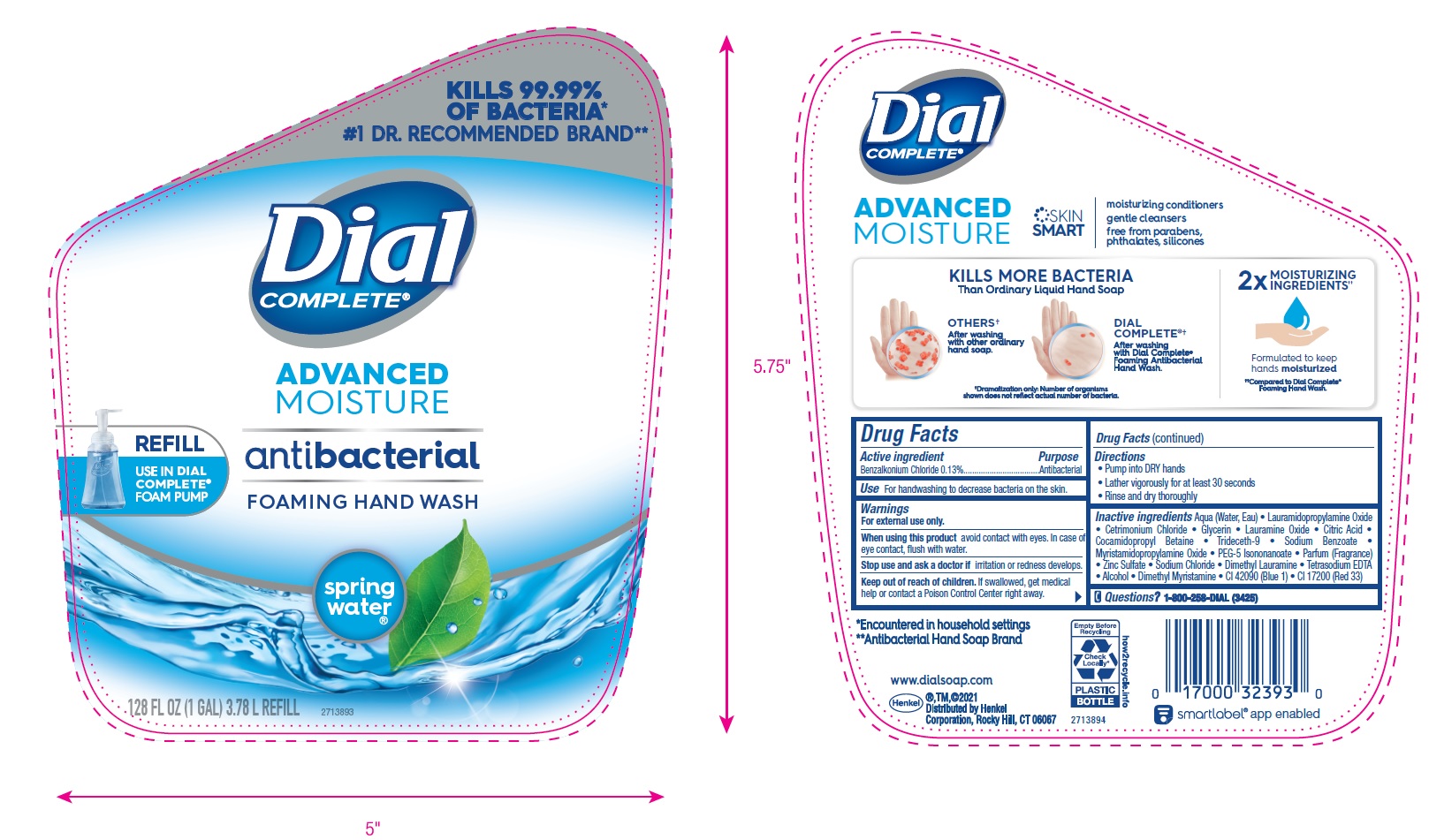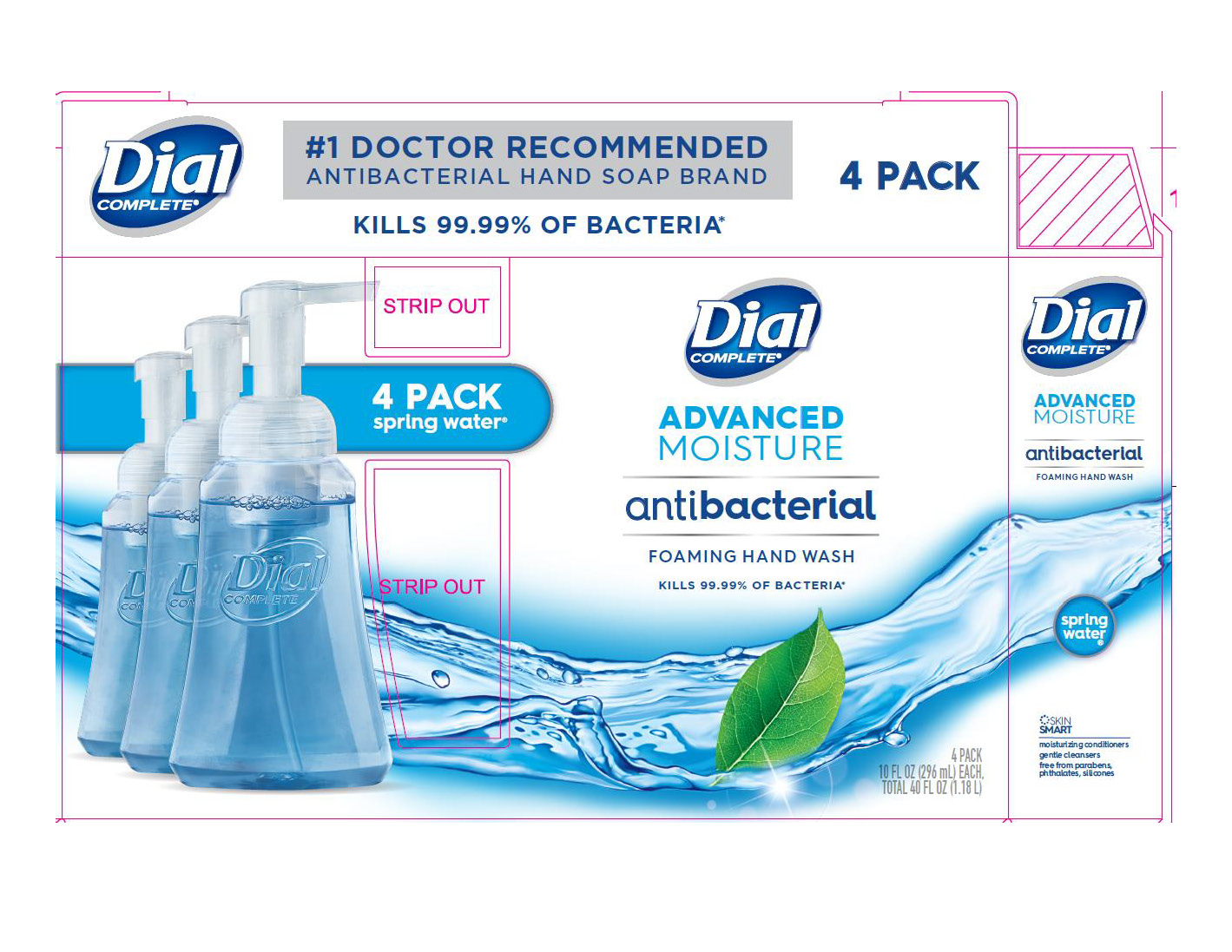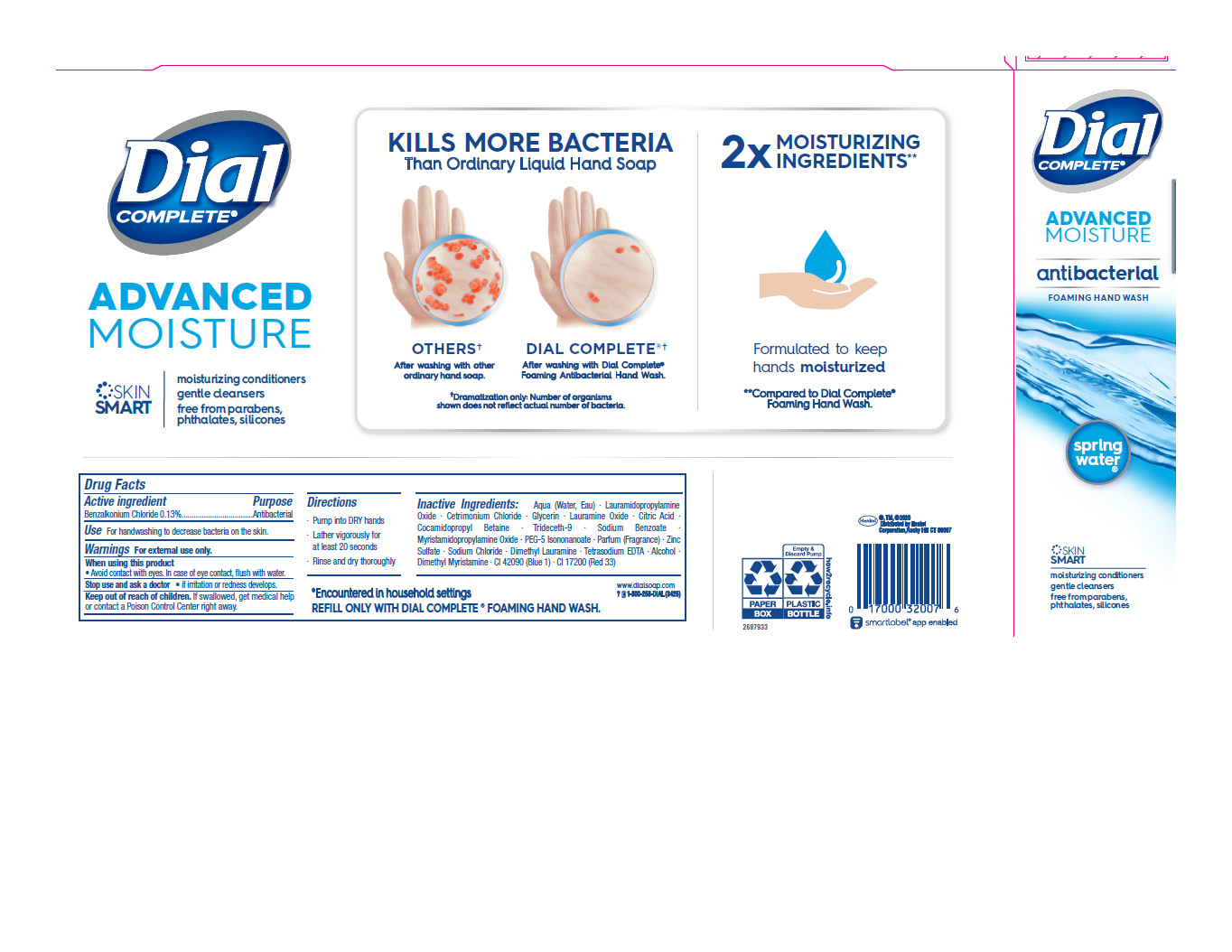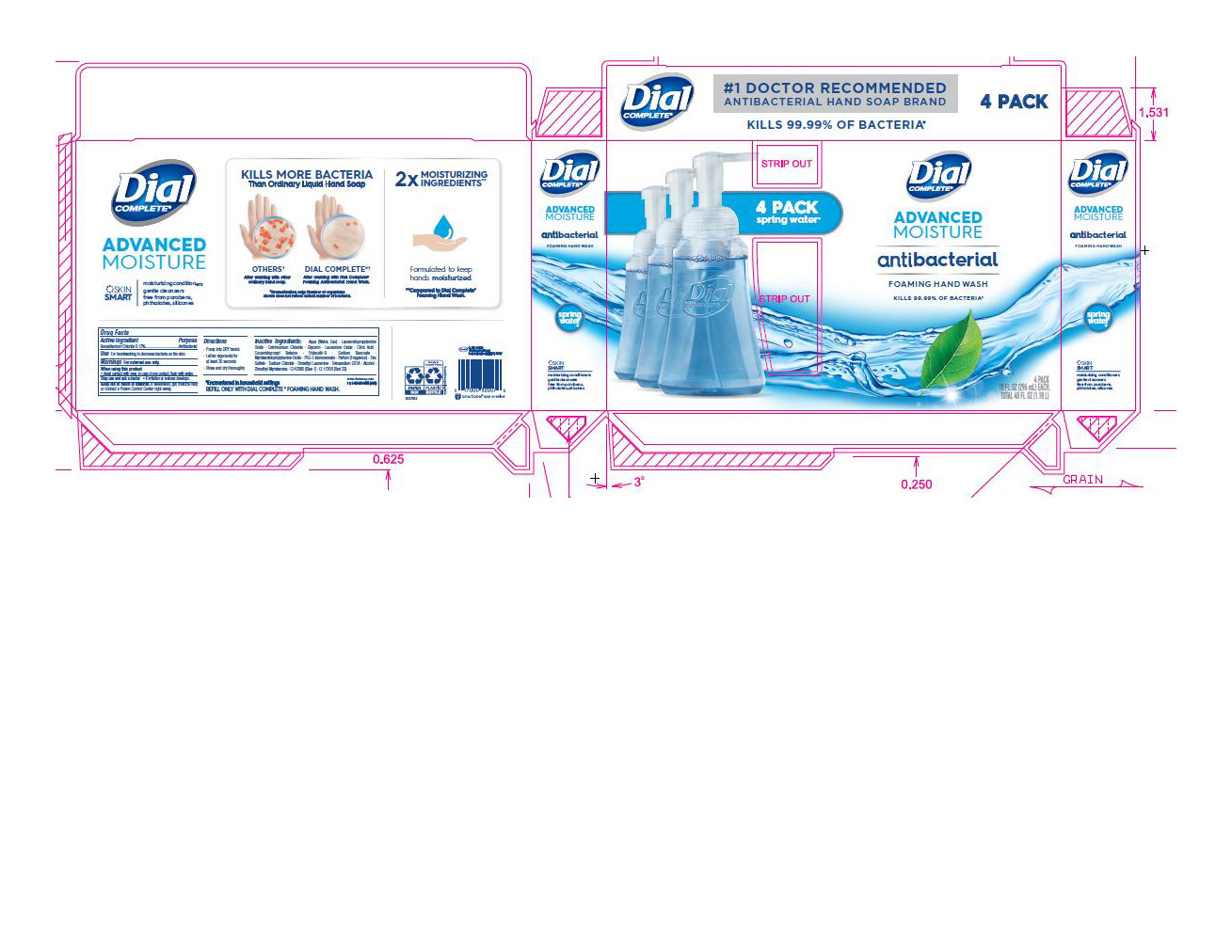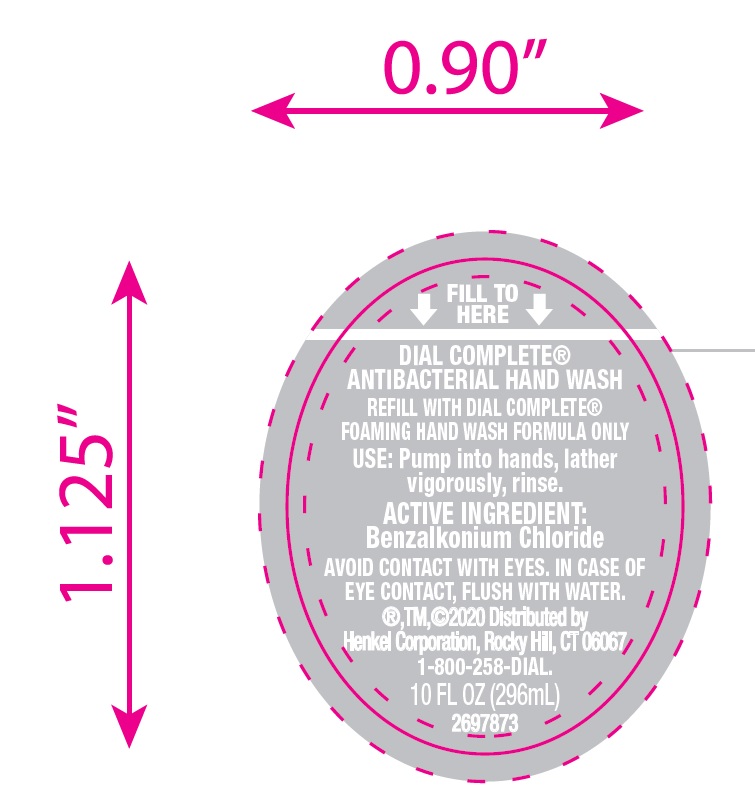 DRUG LABEL: Dial Complete Advanced Moisture Spring Water
NDC: 50663-342 | Form: SOLUTION
Manufacturer: Zotos International Inc
Category: otc | Type: HUMAN OTC DRUG LABEL
Date: 20201109

ACTIVE INGREDIENTS: BENZALKONIUM CHLORIDE 0.13 g/100 mL
INACTIVE INGREDIENTS: WATER 91.51 mL/100 mL

Dial Complete Advanced Moisture -FHW

Active ingredient

Benzalkonium Chloride 0.13%

Purpose

Antibacterial

Uses

For Handwashing to decreases bacteria on the skin.

Warnings

For external use only.

When using this product

Avoid Contact with eyes. In case of eye contact, flush with water.

Stop use and ask doctor if

Irritation or redness develops

Keep out of reach of children.

If swallowed get medical help or contact a Poison Control Center right away.

Directions

Pump into DRY hands.

Later vigorously for at least 20 seconds.

Rinse and dry thoroughly.

Inactive ingredients

Advanced Moisture Spring Water FHW

Aqua (Water, Eau) · Lauramidopropylamine Oxide · Cetrimonium Chloride · Glycerin · Lauramine Oxide · Citric Acid · Cocamidopropyl Betaine · Trideceth-9 · Sodium Benzoate · Myristamidopropylamine Oxide · PEG-5 Isononanoate · Parfum (Fragrance) · Zinc Sulfate · Sodium Chloride · Dimethyl Lauramine · Tetrasodium EDTA · Alcohol · Dimethyl Myristamine · CI 42090 (Blue 1) · CI 17200 (Red 33)

Questions

www.dialsoap.com

call 1-800-258-DIAL(3425)

Legal Entity

®,TM,©2020

Distributed by Henkel

Corporation, Rocky Hill, CT 06067

*Encountered in household settings

REFILL ONLY WITH DIAL COMPLETE FOAMING HAND WASH

INDICATIONS AND USAGE

For handwashing to decrease bacteria on the skin.

Topical Liquid Solution

Foaming Hand wash

4 Pack

10 FL OZ (296mL) EACH

TOTAL 40 FL OZ (1.18 L)